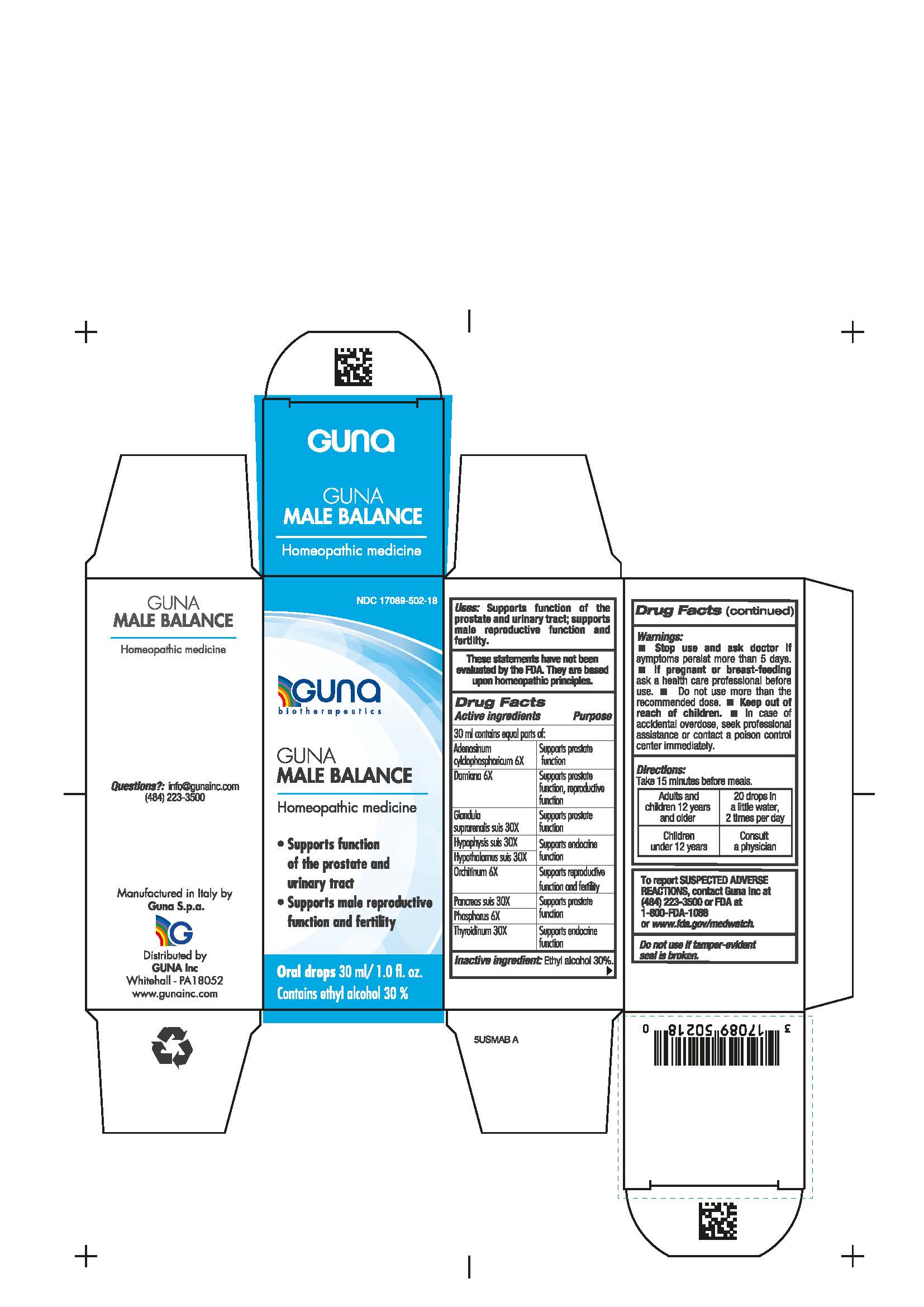 DRUG LABEL: GUNA MALE SUPPORT
NDC: 17089-502 | Form: SOLUTION/ DROPS
Manufacturer: Guna spa
Category: homeopathic | Type: HUMAN OTC DRUG LABEL
Date: 20210212

ACTIVE INGREDIENTS: TURNERA DIFFUSA LEAFY TWIG 6 [hp_X]/30 mL; SUS SCROFA TESTICLE 6 [hp_X]/30 mL; PHOSPHORUS 6 [hp_X]/30 mL; ADENOSINE CYCLIC PHOSPHATE 6 [hp_X]/30 mL; SUS SCROFA PITUITARY GLAND 30 [hp_X]/30 mL; SUS SCROFA HYPOTHALAMUS 30 [hp_X]/30 mL; SUS SCROFA ADRENAL GLAND 30 [hp_X]/30 mL; SUS SCROFA PANCREAS 30 [hp_X]/30 mL; SUS SCROFA THYROID 30 [hp_X]/30 mL
INACTIVE INGREDIENTS: ALCOHOL 9 mL/30 mL

GUNA MALE SUPPORT

USES

Supports function of the prostate and urinary tract; supports male reproductive function and fertility

ACTIVE INGREDIENTS/PURPOSE

Adenosinum cylclophosphoricum 6X Supports prostate function

Damiana 6X Supports prostate function, reproductive function

Glandula suprarenalis suis 30X Supports prostate function

Hypophysis suis 30X Supports endocrine function

Hypothalamus suis 30X Supports endocrine function

Orchitinum 6X Supports reproductive function and fertility

Pancreas suis 30X Supports prostate function

Phosphorus 6X Supports prostate function

Thyroidinum 30X Supports endocrine function

DIRECTIONS

Take 15 minutes before meals.

Adults and children 12 years and older: 20 drops in a little water, 2 times per day

Children under 12 years: consult a physician

Inactive ingredient: Ethyl alcohol 30%.

QUESTIONS

info@gunainc.com
Tel. (484) 223-3500

WARNINGS

Keep out of reach of children.

INDICATIONS AND USAGE

Take 15 minutes before meals.

PREGNANCY

If pregnant or breast-feeding ask a health care profesisonal before use.

WARNINGS

- Stop use and ask doctor if symptoms worsen or persist more than 5 days.
- If pregnant or breast-feeding ask a health care professional before use.
- Keep out of reach of children.
- In case of accidental overdose, seek professional assistance or contact a poison control center immediately
- Contains ethyl alcohol 30%